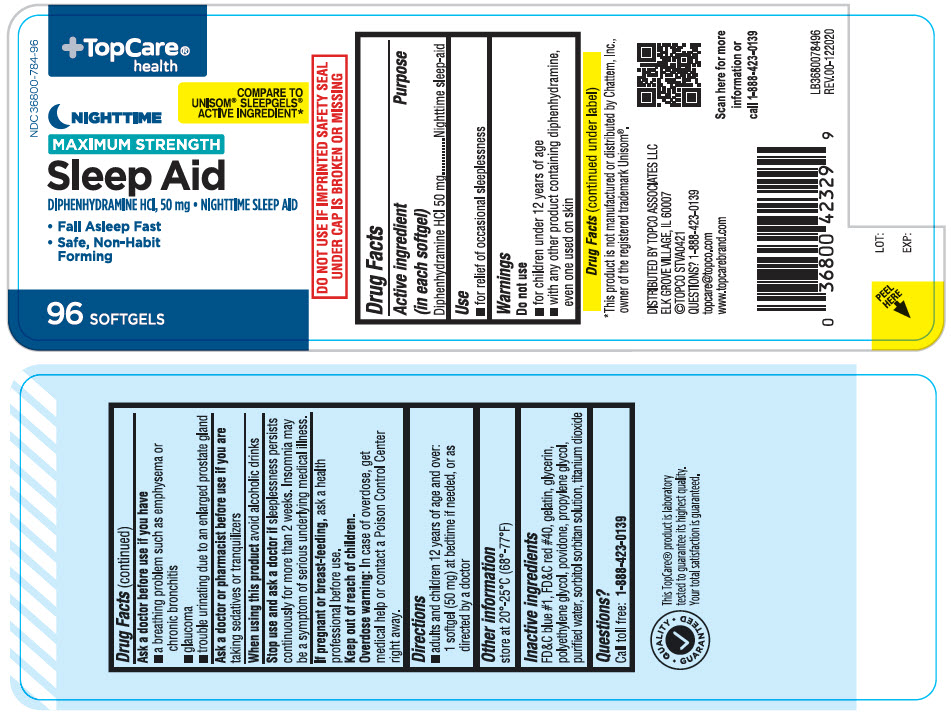 DRUG LABEL: Sleep Aid Nighttime
NDC: 36800-784 | Form: CAPSULE, LIQUID FILLED
Manufacturer: TOPCO ASSOCIATES LLC
Category: otc | Type: HUMAN OTC DRUG LABEL
Date: 20241231

ACTIVE INGREDIENTS: DIPHENHYDRAMINE HYDROCHLORIDE 50 mg/1 1
INACTIVE INGREDIENTS: FD&C BLUE NO. 1; FD&C RED NO. 40; GELATIN, UNSPECIFIED; GLYCERIN; POLYETHYLENE GLYCOL, UNSPECIFIED; POVIDONE K30; PROPYLENE GLYCOL; WATER; SORBITOL; SORBITAN; TITANIUM DIOXIDE

Sleep Aid Nighttime

Active ingredient (in each softgel)

Diphenhydramine HCl 50 mg

Purpose

Nighttime sleep-aid

Use

• for relief of occasional sleeplessness

Warnings

Do not use
• for children under 12 years of age
• with any other product containing diphenhydramine, even one used on skin

Ask a doctor before use if you have
• a breathing problem such as emphysema or chronic bronchitis
• glaucoma
• trouble urinating due to an enlarged prostate gland

Ask a doctor or pharmacist before use if you are
taking sedatives or tranquilizers

When using this product avoid alcoholic drinks

Stop use and ask a doctor if sleeplessness persists continuously for more than 2 weeks. Insomnia may be a symptom of serious underlying medical illness.

If pregnant or breast-feeding, ask a health professional before use.

Keep out of reach of children.
Overdose warning: In case of overdose, get medical help or contact a Poison Control Center right away.

Directions

• adults and children 12 years of age and over: 1 softgel (50 mg) at bedtime if needed, or as directed by a doctor

Other information

store at 20°-25°C (68°-77°F)

Inactive ingredients

FD&C blue #1, FD&C red #40, gelatin, glycerin, polyethylene glycol, povidone, propylene glycol, purified water, sorbitol sorbitan solution, titanium dioxide

Questions?

Call toll free: 1-888-423-0139

TopCare®
health

MAXIMUM STRENGTH

• Fall Asleep Fast
• Safe, Non-Habit Forming

COMPARE TO UNISOM® SLEEPGELS® ACTIVE INGREDIENT*

DO NOT USE IF IMPRINTED SAFETY SEAL UNDER CAP IS BROKEN OR MISSING

*This product is not manufactured or distributed by Chattem, Inc., owner of the registered trademark Unisom®.

DISTRIBUTED BY TOPCO ASSOCIATES LLC
ELK GROVE VILLAGE, IL 60007
©TOPCO STVA0421 topcare@topco.comwww.topcarebrand.com

This TopCare® product is laboratory tested to guarantee its highest quality. Your total satisfaction is guaranteed.